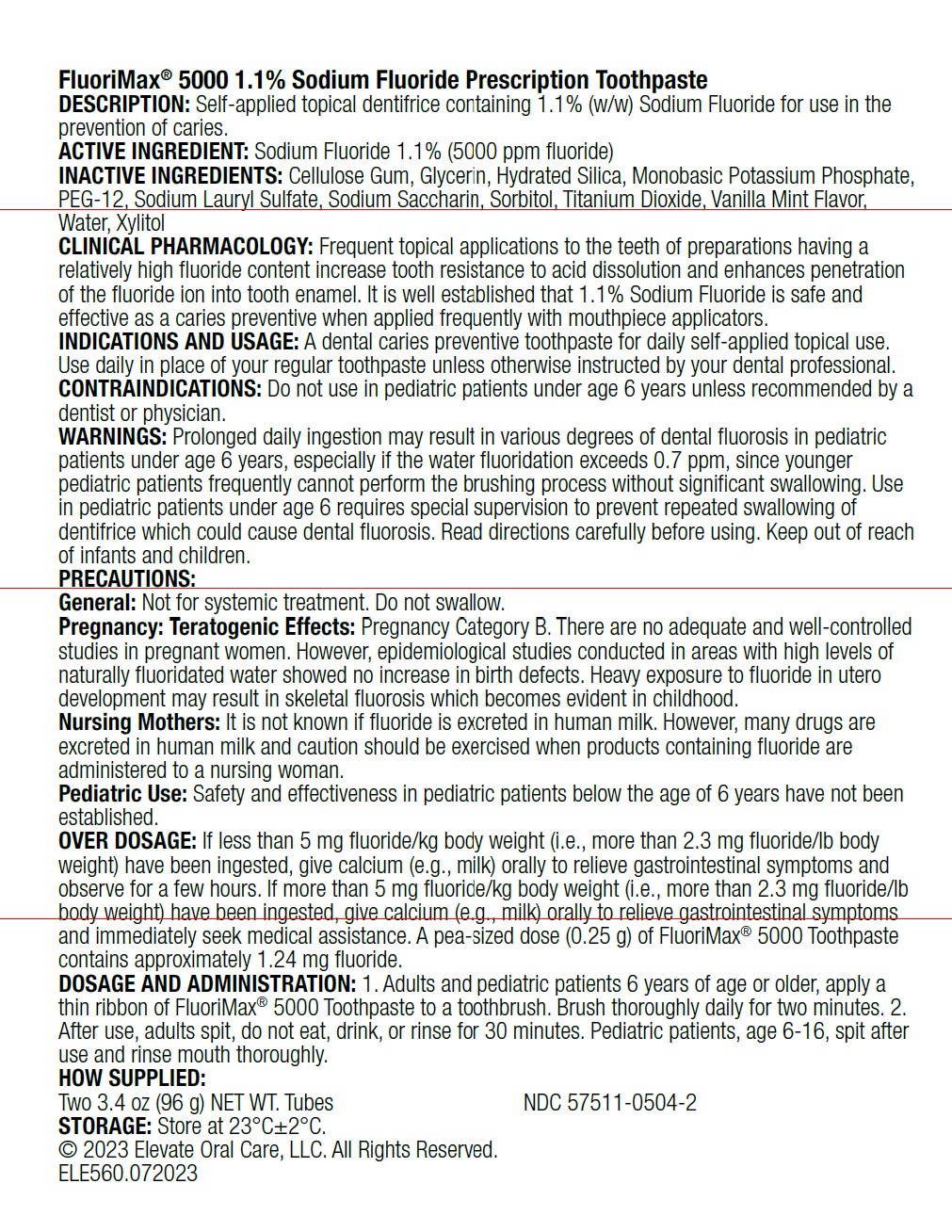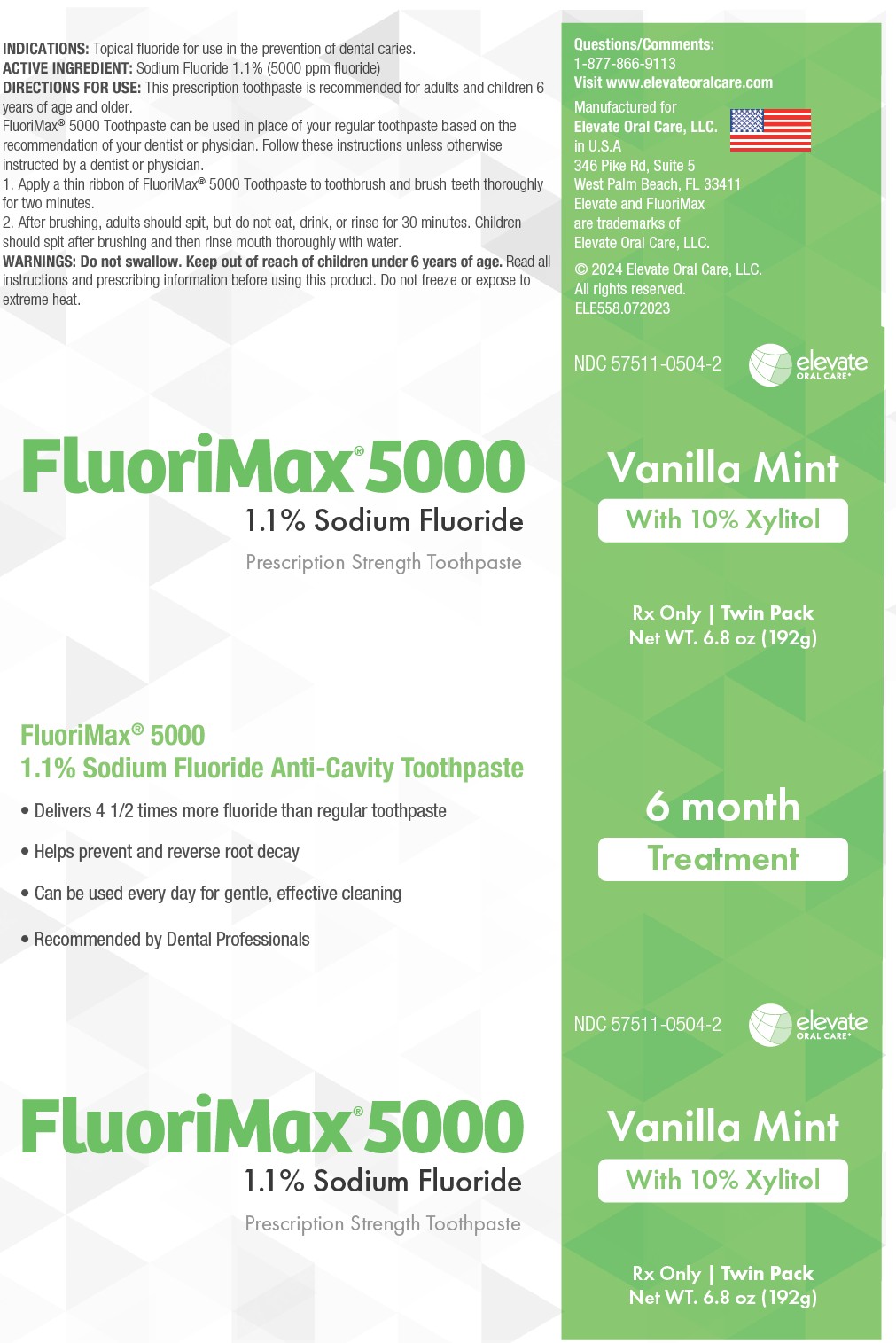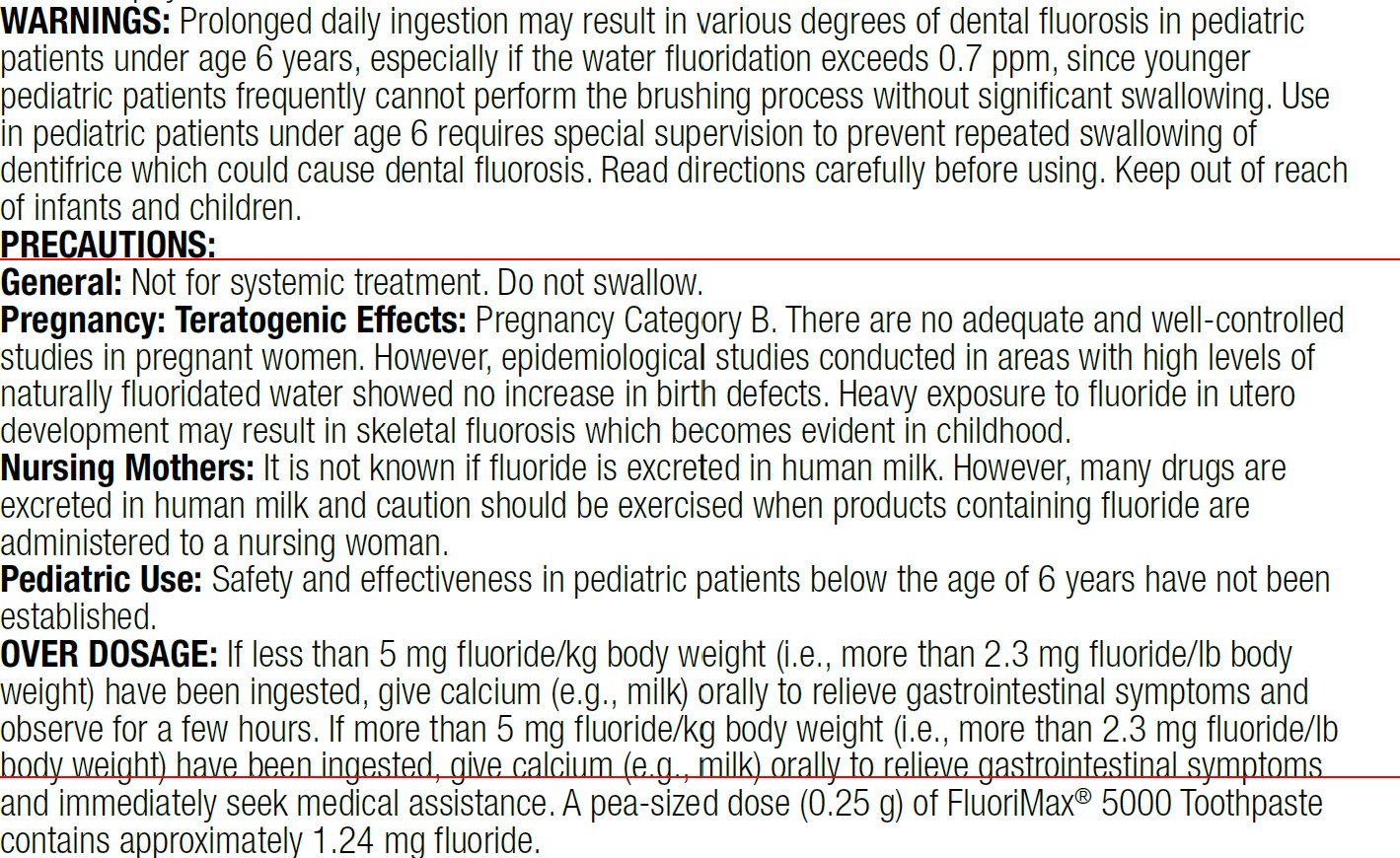 DRUG LABEL: FluoriMax 5000
NDC: 57511-0504 | Form: PASTE, DENTIFRICE
Manufacturer: Elevate Oral Care
Category: prescription | Type: HUMAN PRESCRIPTION DRUG LABEL
Date: 20250919

ACTIVE INGREDIENTS: SODIUM FLUORIDE 1.1 g/100 g
INACTIVE INGREDIENTS: XYLITOL; GLYCERIN; HYDRATED SILICA; POTASSIUM PHOSPHATE, MONOBASIC; SACCHARIN; SORBITOL

FluoriMax 5000 1.1% Sodium Fluorida Toothpaste Vanilla Mint Twin Pack